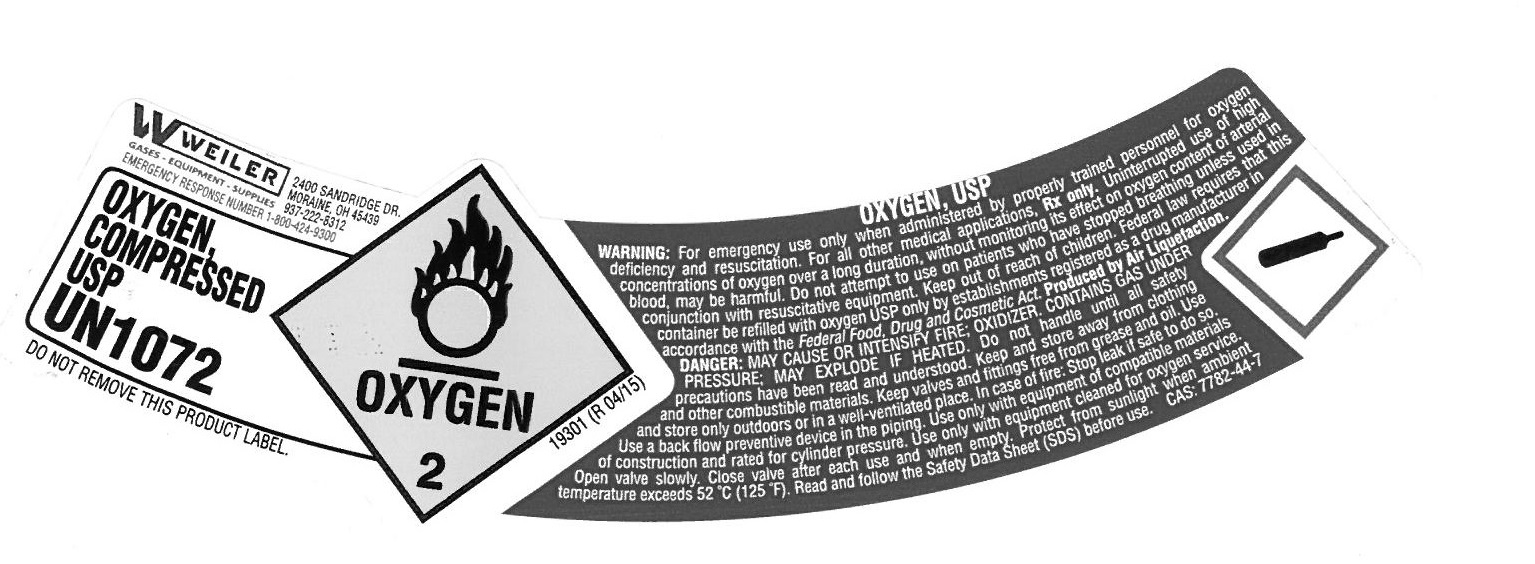 DRUG LABEL: Oxygen
                
NDC: 48664-002 | Form: GAS
Manufacturer: Weiler Welding Company
Category: prescription | Type: HUMAN PRESCRIPTION DRUG LABEL
Date: 20161004

ACTIVE INGREDIENTS: Oxygen 992 L/1000 L

OXYGEN, COMPRESSED

PACKAGE LABEL

Weiler Welding, Inc.
2400 Sandridge Dr,
Moraine, OH 45439
937-222-8312
EMERGENCY RESPONSE NUMBER 1-800-424-9300
UN1072

DO NOT REMOVE THIS PRODUCT LABEL

[OXYGEN 2 SYMBOL] 19301 (R04/15)

OXYGEN* USP

WARNING: For emergency use only when administered by properly trained personnel for Oxygen deficiency and resuscitation. For all other medical applications, Rx only. Uninterrupted use of high concentrations of Oxygen over a long duration, without monitoring its effect on oxygen content of arterial blood, may be harmful. Do not attempt to use on patients who have stopped breathing unless used in conjunction with resuscitative equipment. Keep out of reach of children. Federal law requires that this container be refilled with oxygen USP only by establishments registered as a drug manufacturer in accordance with the Federal Food, Drug and Cosmetic Act. Produced by Air Liquefaction.
DANGER: MAY CAUSE OR INTENSIFY FIRE; OXIDIZER. CONTAINS GAS UNDER PRESSURE; MAY EXPLODE IF HEATED. Do not handle until all safety precautions have been read and understood. Keep and store away from clothing and other combustible materials. Keep valves and fittings free from grease and oil. Use and store only outdoors or in a well-ventilated place. In case of fire: Stop leak if safe to do so. Use a back flow preventive device in the piping. Use only with equipment of compatible materials of construction and rated for cylinder pressure. Use only with equipment cleaned for oxygen service. Open valve slowly. Close valve after each use and when empty. Prtect from sunlight when ambient temperature exceeds 52 degrees C (125 degrees F). Read and follow the Safety Data Sheet (SDS) berfore use.

CAS: 7782-44-7

[COMPRESSED GAS SYMBOL]